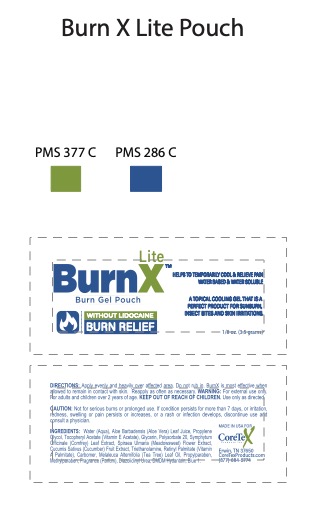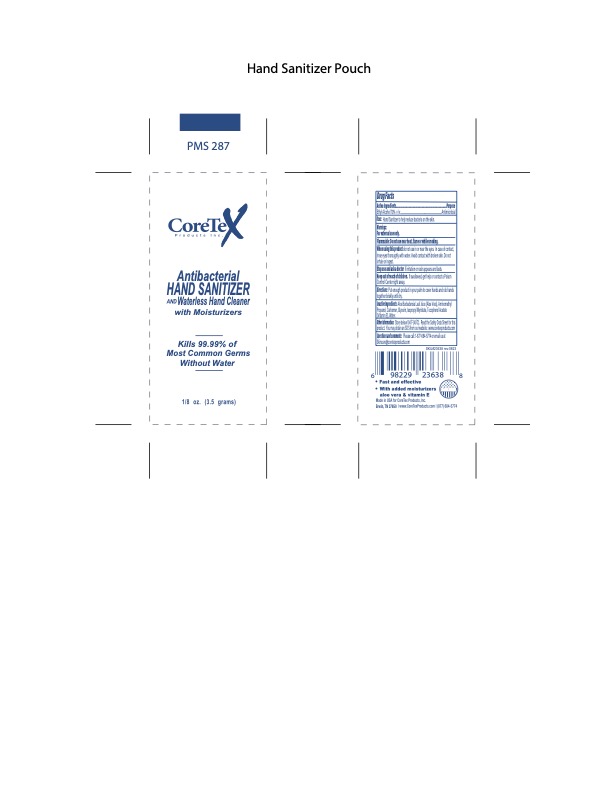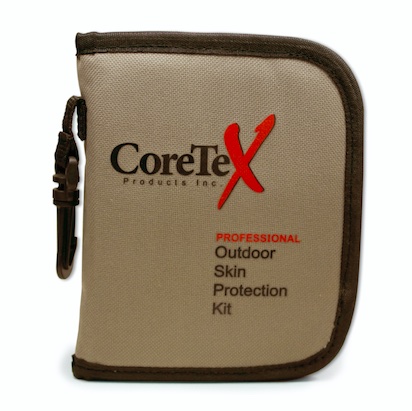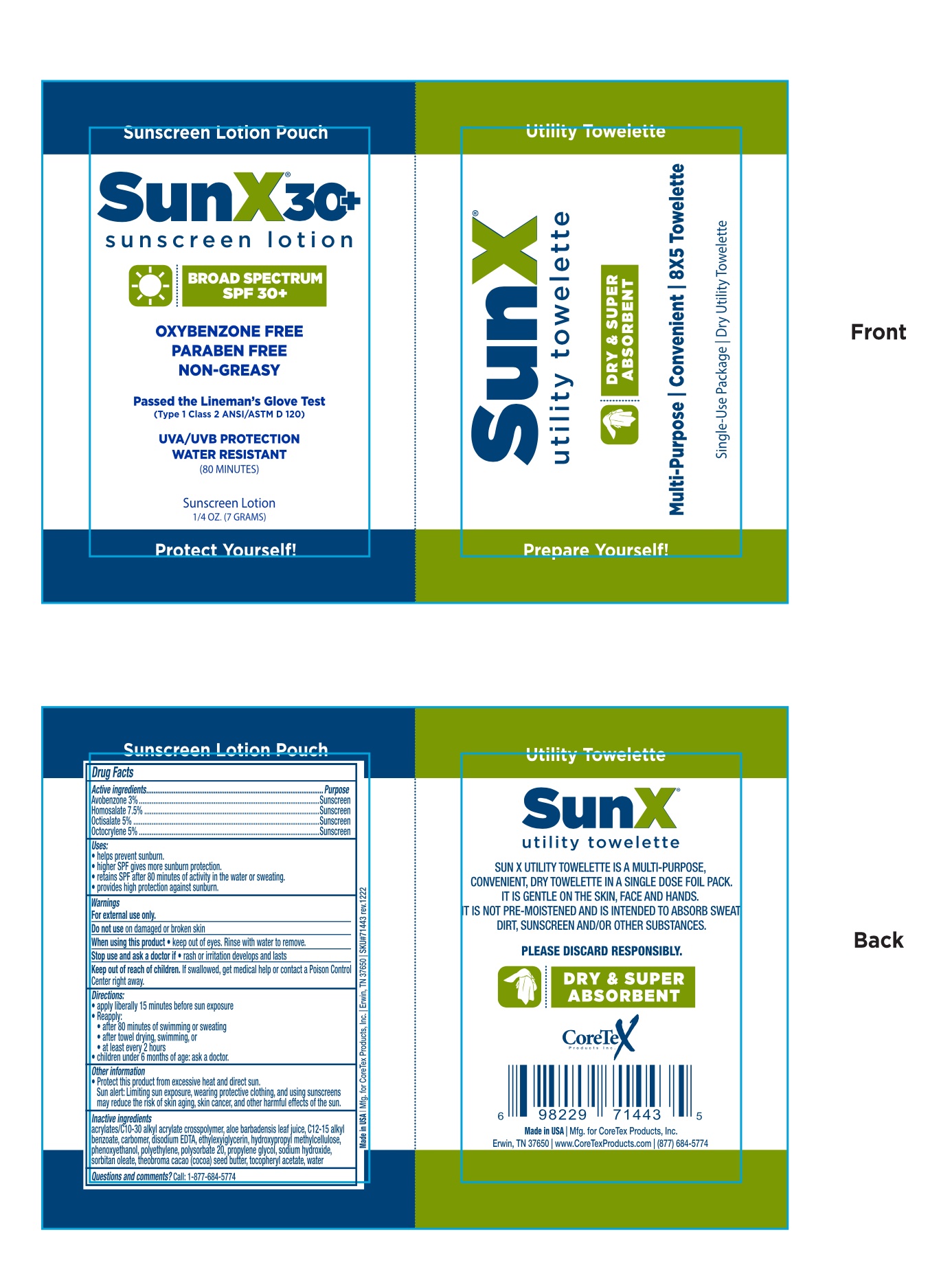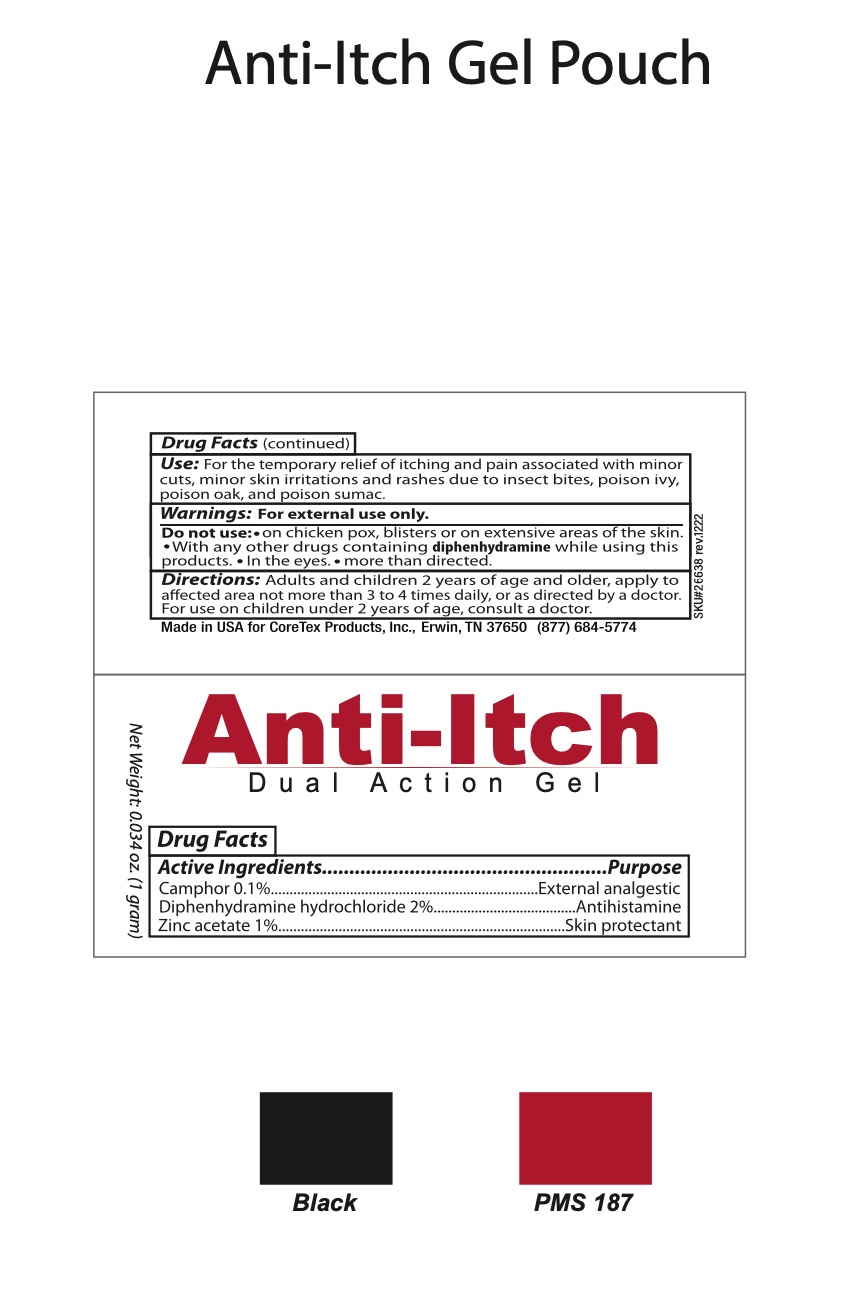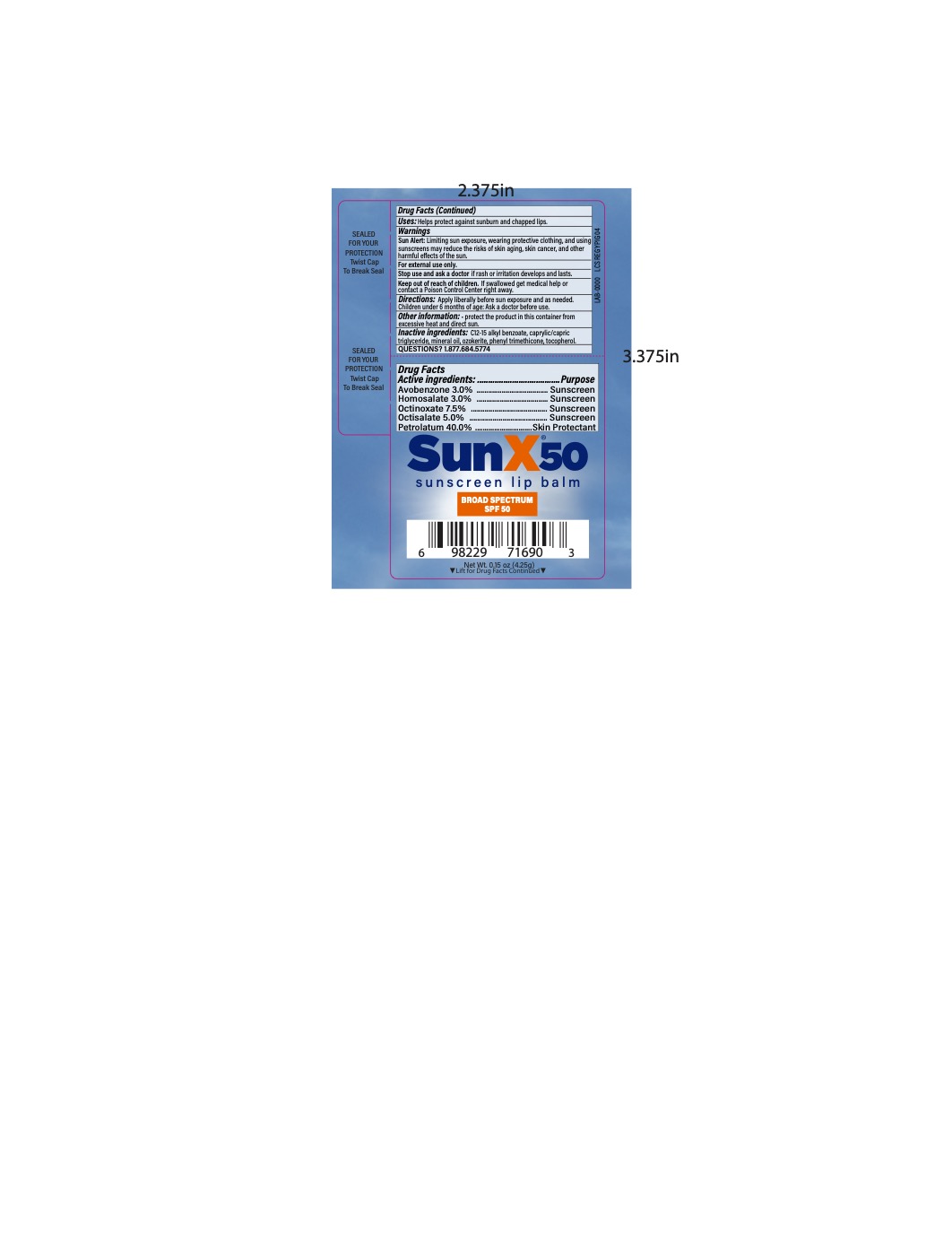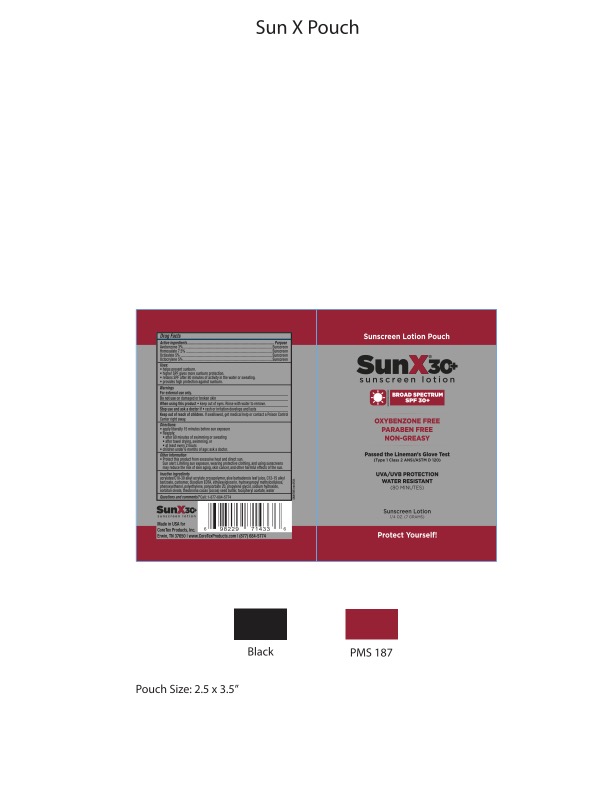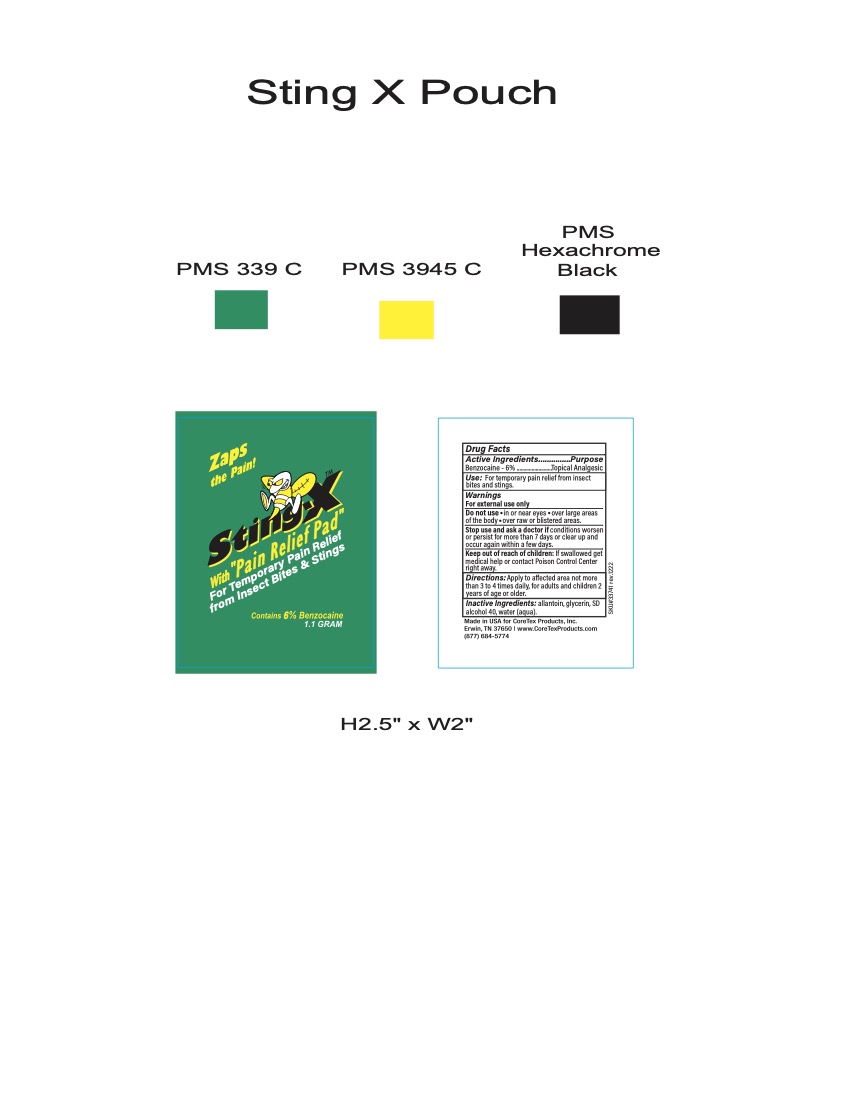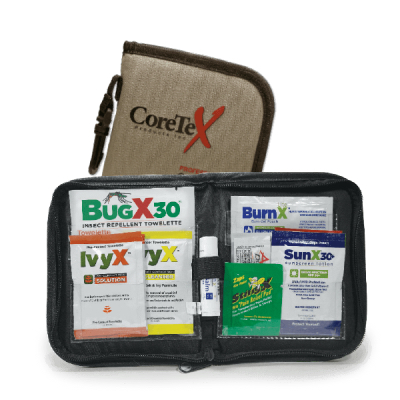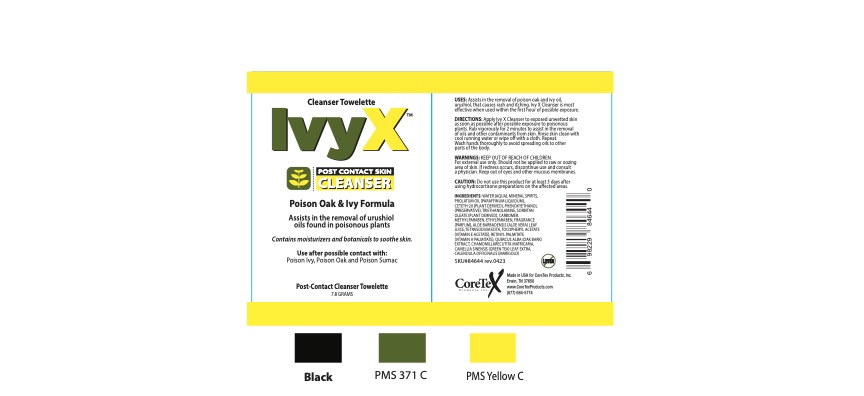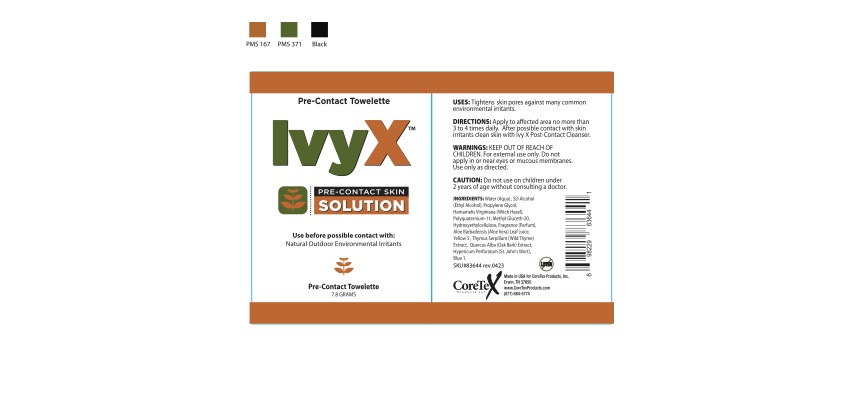 DRUG LABEL: CoreTex Professional Outdoor Skin Protection Wallet
NDC: 65753-514 | Form: KIT | Route: TOPICAL
Manufacturer: CoreTex Products Inc
Category: otc | Type: HUMAN OTC DRUG LABEL
Date: 20251009

ACTIVE INGREDIENTS: HOMOSALATE 7.5 g/100 mL; OCTISALATE 5 g/100 mL; AVOBENZONE 3 g/100 mL; OCTOCRYLENE 5 g/100 mL; AVOBENZONE 3 g/100 g; OCTOCRYLENE 5 g/100 g; OCTISALATE 5 g/100 g; HOMOSALATE 7.5 g/100 g; OCTINOXATE 7.5 g/100 mL; HOMOSALATE 3 g/100 mL; OCTISALATE 5 g/100 mL; AVOBENZONE 3 g/100 mL; PETROLATUM 40 g/100 mL; CAMPHOR (SYNTHETIC) 0.1 g/100 mL; ZINC ACETATE 1 g/100 mL; DIPHENHYDRAMINE HYDROCHLORIDE 2 g/100 mL; BENZOCAINE 6 g/100 mL; ALCOHOL 70 mL/100 mL
INACTIVE INGREDIENTS: ACRYLATES CROSSPOLYMER-6; ALKYL (C12-15) BENZOATE; .ALPHA.-TOCOPHEROL ACETATE; ALOE VERA LEAF; WATER; PHENOXYETHANOL; PEG-6 SORBITAN OLEATE; PROPYLENE GLYCOL PROPYL ETHER; MEDIUM DENSITY POLYETHYLENE; DISODIUM EDTA-COPPER; THEOBROMA CACAO WHOLE; ETHYLHEXYLGLYCERIN; POLYSORBATE 20; METHYLCELLULOSE, UNSPECIFIED; CARBOMER HOMOPOLYMER, UNSPECIFIED TYPE; SODIUM HYDROXIDE; DISODIUM EDTA-COPPER; SODIUM HYDROXIDE; ETHYLHEXYLGLYCERIN; POLYSORBATE 20; METHYLCELLULOSE, UNSPECIFIED; PROPYLENE GLYCOL PROPYL ETHER; CARBOMER HOMOPOLYMER, UNSPECIFIED TYPE; ALOE VERA LEAF; .ALPHA.-TOCOPHEROL ACETATE; WATER; PHENOXYETHANOL; PEG-6 SORBITAN OLEATE; ALKYL (C12-15) BENZOATE; MEDIUM DENSITY POLYETHYLENE; ACRYLATES CROSSPOLYMER-6; THEOBROMA CACAO WHOLE; PHENYL TRIMETHICONE; COCONUT OIL; ALKYL (C12-15) BENZOATE; MINERAL OIL; WHITE WAX; TOCOPHEROL; SODIUM CITRATE; METHYLPARABEN; ANHYDROUS CITRIC ACID; GLYCERIN; DIAZOLIDINYL UREA; METHYLCELLULOSE (1500 CPS); PROPYLPARABEN; ALCOHOL; WATER; PROPYLENE GLYCOL 1-ALLYL ETHER; WATER; ALLANTOIN; GLYCERIN; ALCOHOL; ALOE VERA LEAF; GLYCERIN; ALPHA-TOCOPHEROL ACETATE; WATER; AMINOMETHYL PROPANEDIOL; CARBOMER HOMOPOLYMER, UNSPECIFIED TYPE; ISOPROPYL MYRISTATE

CoreTex Professional Outdoor Skin Protection Wallet and refill
65753-514

Hand Sanitizer Active Ingredients:

SD Alcohol 40-B 62.5%

Hand Sanitizer Purpose

Antimicrobial

Hand Sanitizer Uses:

Hand Sanitizer to help reduce bacteria on the skin.

Hand Sanitizer Warnings

Flammable. Keep away from heat or flame.

For external use only.

When using this product

do not use in or near the eyes. In case of contact, rinse eyes thoroughly with water.

Stop use and ask a doctor

if irritation or rash appears and lasts.

Keep out of reach of children.If swallowed, get help or contact a Poison Control Center right away.

Hand Sanitizer Directions:

Put enough product in your palm to cover hands and rub hands together briskly until dry.

Hand Sanitizer Inactive Ingredients:

actinidia chinesis (kiwi) extract, aloe barbadenis leaf juice, aminomethyl propanol, brassica oleracea italica (broccoli) extract, cannabis sativa (hemp) seed extract, carbomer citrullus vulgaris (watermelon) fruit extract, euterpe oleracea fruit extract, fragaria vesca (strawberry) fruit extract, glycerin, helianthus annus (sunfloer) seed oil, hippophae rhamnoides (sea buckthorn) fruit extract, lycium barbarum (goji) extract, myrciaria dubia (camu camu) fruit extract, propanediol, propylene glycol, punica granatum extract, rubus idaeus seed extract, tocopherol acetate (vitamin E acetate), vaccinium angustifolium (blueberry) extract, vaccinium macrocarpon (cranberry) fruit extract, vitis vinifera (grape) seed extra, water

Hand Sanitizer Other Information:

Store below 110oF (43o), Read the Safety Data Sheet for this Product. You may obtain an SDS from our website: www.coretexproducts.com or Call: 1-877-684-5774

SunX 30 Active Ingredients:

Avobenzone 3.0%

Homosalate 7.5%

Octisalate 5.0%

Octocrylene 5.0%

SunX 30 Purpose

Sunscreen

Sunscreen

Sunscreen

Sunscreen

SunX 30 Uses:

- helps prevent sunburn.
- higher SPF gives more sunburn protection.
- retains SPF after 80 minutes of activity in the water or sweating.
- provides high protection against sunburn.

SunX 30 Warnings

For external use only

SunX 30 Do Not Use

- on damaged or broken skin

When using this product

- keep out of the eyes
- rinse with water to remove

Stop use and ask a doctor if

- rash or irritation develops and lasts

Keep out of reach of children.

If swallowed, get medical help or contact Poison Control Center right away.

SunX 30 Directions:

- apply liberally and evenly 15 minutes before sun exposure
- reapply:
- after 80 minutes of swimming or sweating
- after towel drying, swimming, or
- at least every 2 hours
- children under 6 months of age: Ask a doctor

SunX 30 Other Information:

- protect this product from excessive heat or direct sun.

Sun alert: Limiting sun exposure, wearing protective clothing, and using sunscreens may reduce the risk of skin aging, skin cancer, and other harmful effects of the sun.

SunX 30 Inactive Ingredients:

acrylates/C10-30 alkyl acrylate crosspolymer, aloe barbadensis leaf juice, C12-15 alkyl benzoate, carbomer, disodium EDTA, ethylexyiglycerin, hydroxypropyl methylcellulose, phenoxyethanol, polyethylene, polysorbate 20, propylene glycol, sodium hydroxide, sorbitan oleate, theobroma cacao (cocoa) seed butter, tocopheryl acetate, water

SunX 30 Questions?

Call: 1-877-684-5774

SunX 50 Lip Balm Active Ingredients:

Avobenzone…3.0%

Homosalate…3.0%

Octinoxate...7.5%

Octisalate…5.0%

Petrolatum...40.0%

SunX 50 Lip Balm Purpose

Sunscreen

Sunscreen

Sunscreen

Sunscreen

Skin Protectant

SunX 50 Lip Balm Uses:

Helps protect against sunburn and chapped lips.

SunX 50 Lip Balm Warnings

Sun Alert:Limiting sun exposure, wearing protective clothing, and using sunscreens may reduce the risks of skin aging, skin cancer, and other harmful effects of the sun.

Do not use

Do not useon damaged or broken skin.

Stop use and ask a doctor if

- rash occurs

When using this product

- keep out of eyes. Rinse to remove.

Keep out of reach of children. If swallowed, get medical help or contact a Poison Control Center right away.

SunX 50 Lip Balm Directions:

- Apply liberally before sun exposure and as needed
- Children under 6 months of age: Ask a doctor before use.

SunX 50 Lip Balm Other information:

protect the product in this container from excessive heat and direct sun.

SunX 50 Lip Balm Inactive Ingredients:

C12-15 alkyl benzoate, caprylic/capric triglyceride, mineral oil, ozokerite, phenyl trimethicone, tocopherol.

Anti-Itch Active Ingredients:

Camphor 0.1%

Diphenhydramine hydrochloride 2%

Zinc acetate 1%

Anti-Itch Purpose

Extrenal analgesic

Antihistamine

Skin protectant

Anti-Itch Uses:

- For the temporary relief of itching and pain associated with minor skin irritations and rashes due to insect bites, poison ivy, poison oak, poison sumac.
- dries the oozing and weeping of poison ivy, poison oak, poison sumac.

Anti-Itch Warnings

For external use only

Do Not Use

- on chicken pox, blisters or on extensive areas of the skin
- with any drugs containing diphenhydramine while using this product.

When using this product

- keep out of eyes.

Stop use and ask a doctor if

- conditions worsen or if symptoms persist for more than 7 days or clear up and occur again within a few days.

Keep out of reach of children

If swallowed get medical help or contact Poison Control center right away.

Anti-Itch Directions:

- Adults and children 12 years of age and older, apply to affected area not more than 3 to 4 times daily, or as directed bu a doctor.

Anti-Itch Other Information:

- protect this product from excessive heat and direct sun.

Anti-Itch Inactive Ingredients:

citric acid, diazolidinyl urea, glycerin, hydroxypropyl methylcellulose, methylparaben, propylene glycol, propylparaben, SD alcohol 40, sodium citrate, water (aqua).

Anti-Itch Questions?

Call: 1-877-684-5774

Sting X Active Ingredients:

Benzocaine 6%

Sting X Purpose

Topical Analgesic

Sting X Use:

For temporary pain relief from insect bites and stings

Sting X Warnings

For external use only

Do not use

- in or near eyes
- over large areas of the body
- over raw or blistered areas

Stop use and ask a doctor if

- conditions worsen or persist for more than 7 days or clear up and occur again within a few days

Keep out of reach of children.

If swallowed get medical help or contact Poison Control center right away.

Sting X Directions:

Apply to affected area not more than 3 to 4 times daily, for adults and children 2 years of age or older.

Sting X Inactive Ingredients:

SD alcohol 40, water (aqua), glycerin, allantoin

Sting X Other Information:

Made in USA for CoreTex Products, Inc.

Bakersfield, CA 93308

www.CoreTexProducts.com (877)684-5774

Outdoor Professional Kit and Refill Kit Contents

1 ea – Sun X SPF 30 Broad Spectrum Lotion Pouch

1 ea – Sun X SPF 30 Broad Spectrum Multi-Pack Pouch w/Towelette
1 ea – Sun X SPF 30 Lip Balm
2 ea – Bug X 30 Insect Repellent Towelette
2 ea – Ivy X Pre-Contact Barrier Towelette
2 ea – Ivy X Post-Contact Cleanser Towelette
2 ea – Burn X Lite Cooling Gel Pouch
1 ea – Anti-Itch Gel Pouch
1 ea – Sting X Pain Relief Pad
1 ea – Hand Sanitizer Gel Pouch